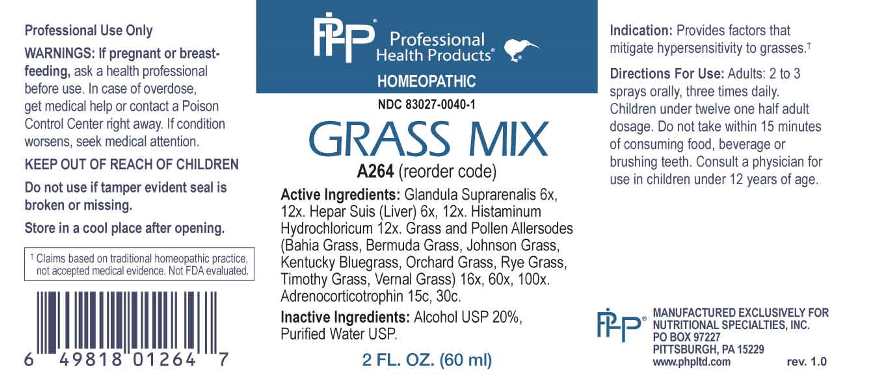 DRUG LABEL: Grass Mix
NDC: 83027-0040 | Form: SPRAY
Manufacturer: Nutritional Specialties, Inc.
Category: homeopathic | Type: HUMAN OTC DRUG LABEL
Date: 20251006

ACTIVE INGREDIENTS: BOS TAURUS ADRENAL GLAND 6 [hp_X]/1 mL; PORK LIVER 6 [hp_X]/1 mL; HISTAMINE DIHYDROCHLORIDE 12 [hp_X]/1 mL; PASPALUM NOTATUM POLLEN 16 [hp_X]/1 mL; CYNODON DACTYLON WHOLE 16 [hp_X]/1 mL; SORGHUM HALEPENSE POLLEN 16 [hp_X]/1 mL; POA PRATENSIS TOP 16 [hp_X]/1 mL; DACTYLIS GLOMERATA TOP 16 [hp_X]/1 mL; LOLIUM PERENNE TOP 16 [hp_X]/1 mL; PHLEUM PRATENSE TOP 16 [hp_X]/1 mL; ANTHOXANTHUM ODORATUM POLLEN 16 [hp_X]/1 mL; CORTICOTROPIN 15 [hp_C]/1 mL
INACTIVE INGREDIENTS: WATER; ALCOHOL

DRUG FACTS:

ACTIVE INGREDIENTS:

Glandula Suprarenalis 6X, 12X, Hepar Suis (Liver) 6X, 12X, Histaminum Hydrochloricum 12X, Bahia Grass 16X, 60X, 100X, Bermuda Grass 16X, 60X, 100X, Johnson Grass 16X, 60X, 100X, Kentucky Bluegrass 16X, 60X, 100X, Orchard Grass 16X, 60X, 100X, Rye Grass 16X, 60X, 100X, Timothy Grass 16X, 60X, 100X, Vernal Grass 16X, 60X, 100X, Adrenocorticotrophin 15C, 30C.

PURPOSE:

Provides factors that mitigate hypersensitivity to grasses.†

†Claims based on traditional homeopathic practice, not accepted medical evidence. Not FDA evaluated.

WARNINGS:

Professional Use Only

If pregnant or breast-feeding, ask a health professional before use.

In case of overdose, get medical help or contact a Poison Control Center right away.

If condition worsens, seek medical attention.

KEEP OUT OF REACH OF CHILDREN

Do not use if tamper evident seal is broken or missing.

Store in a cool place after opening

KEEP OUT OF REACH OF CHILDREN:

In case of overdose, get medical help or contact a Poison Control Center right away.

DIRECTIONS:

Adults: 2 to 3 sprays orally, three times daily. Children under twelve one half adult dosage. Do not take within 15 minutes of consuming food, beverage or brushing teeth. Consult a physician for use in children under 12 years of age.

INDICATIONS:

Provides factors that mitigate hypersensitivity to grasses.†

†Claims based on traditional homeopathic practice, not accepted medical evidence. Not FDA evaluated.

INACTIVE INGREDIENTS:

Alcohol USP 20%, Purified Water USP.

QUESTIONS:

MANUFACTURED EXCLUSIVELY FOR

NUTRITIONAL SPECIALTIES, INC.

PO BOX 97227

PITTSBURG, PA 15229

www.phpltd.com

PACKAGE LABEL DISPLAY:

Professional

Health Products

HOMEOPATHIC

NDC 83027-0040-1

GRASS MIX

2 FL. OZ (60 ml)